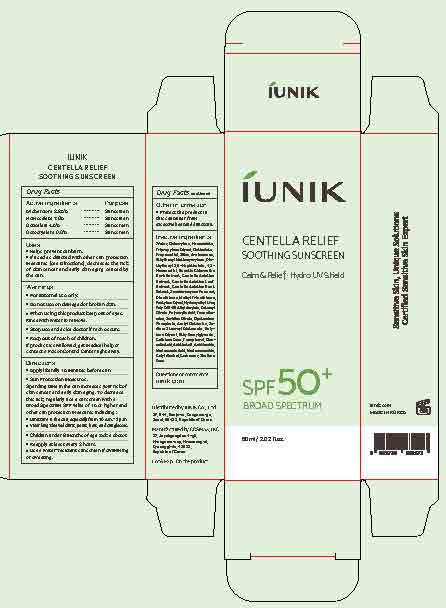 DRUG LABEL: CENTELLA RELIEF SOOTHING SUNSCREEN
NDC: 83403-100 | Form: LOTION
Manufacturer: IUNIK Co., Ltd.
Category: otc | Type: HUMAN OTC DRUG LABEL
Date: 20260107

ACTIVE INGREDIENTS: OCTOCRYLENE 9 g/100 mL; AVOBENZONE 2.85 g/100 mL; HOMOSALATE 7 g/100 mL; OCTISALATE 4.5 g/100 mL
INACTIVE INGREDIENTS: TRIPROPYLENE GLYCOL; MADECASSOSIDE; POLYACRYLIC ACID (8000 MW); WATER; DIMETHICONE; METHYL TRIMETHICONE; CARBOMER; CENTELLA ASIATICA ROOT; ASIATICOSIDE; SACCHAROMYCES CEREVISIAE; SILICA; MADECASSIC ACID; TOCOPHEROL; PROPANEDIOL; BEHENYL ACRYLATE POLYMER; CETYL ALCOHOL; SODIUM STEAROYL GLUTAMATE; CELLULOSE GUM; 1,2-HEXANEDIOL; CENTELLA ASIATICA TRITERPENOIDS; OLEANOLIC ACID; ASIATIC ACID; ETHYLHEXYL METHOXYCRYLENE; DIETHYLHEXYL 2,6-NAPHTHALATE; HYDROXYETHYL UREA; CETEARYL OLIVATE; TROMETHAMINE; SORBITAN OLIVATE; ACETYL GLUTAMINE; XANTHAN GUM; ANNICKIA CHLORANTHA BARK; CENTELLA ASIATICA; PENTYLENE GLYCOL; DIBASIC POTASSIUM PHOSPHATE; BUTYLENE GLYCOL; ETHYLHEXYLGLYCERIN

CENTELLA RELIEF SOOTHING SUNSCREEN

ACTIVE INGREDIENTS

Avobenzone 2.84%

Homosalate 7.0 %

Octisalate 4.5%

Octocrylene 9.0%

PURPOSE

Sunscreen

USES

- Helps prevent sunburn.

- If used as directed with other sun protection measures (see Directions), decrease the risk of skin cancer and early skin aging caused by the sun.

WARNINGS

- For external use only.
- Do not use on damaged or broken skin.
- When using this product, keep out of eyes. Rinse with water to remove.
- Stop use and ask a doctor if rash occurs.
- Keep out of reach of children. If swallowed, get medical help or contact a Poison Control Center right away.

KEEP OUT OF REACH OF CHILDREN

- If product is swallowed, get medical help or contact a Poison Control Center right away.

DIRECTIONS

- Apply liberally 15 minutes before sun exposure.
- Sun protection measures.
  - Spending time in the sun increases your risk of skin cancer and early skin aging. To decrease this risk, regularly use a sunscreen with a Broad Spectrum SPF value of 15 or higher and other sun protection measures including:
- Limit time in the sun, especially from 10 a.m.–2 p.m.
- Wear long-sleeved shirts, pants, hats, and sunglasses.
- Children under 6 months of age: Ask a doctor.
- Reapply at least every 2 hours.
- Use a water resistant sunscreen if swimming or sweating.

INACTIVE INGREDIENTS

Water, Tripropylene Glycol, Propanediol, Silica, Ethylhexyl Methoxycrylene, Diethylhexy 2,6-Naphthalate, 1,2-Hexanediol, Enantia Chlorantha Bark Extract, Centella Asiatica Extract, Centella Asiatica Leaf Extract, Centella Asiatica Root Extract, Saccharomyces Ferment, Dimethicone, Methyl Trimethicone, Pentylene Glycol, Hydroxyethyl Urea, Poly C10-30 Alky Acrylate, Cetearyl Olivate, Polyacrylic Acid, Tromethamine, Sorbitan Olivate, Dipotassium Phosphate, Acetyl Glutamine, Sodium Stearoyl Glutamate, Butylene Glycol, Ethylhexylglycerin, Cellulose Gum, Tocopherol, Oleanolic Acid, Asiatic Acid, Asiaticoside, Madecassic Acid, Madecassoside, Cetyl Alcohol, Carborer, Xanthan Gum